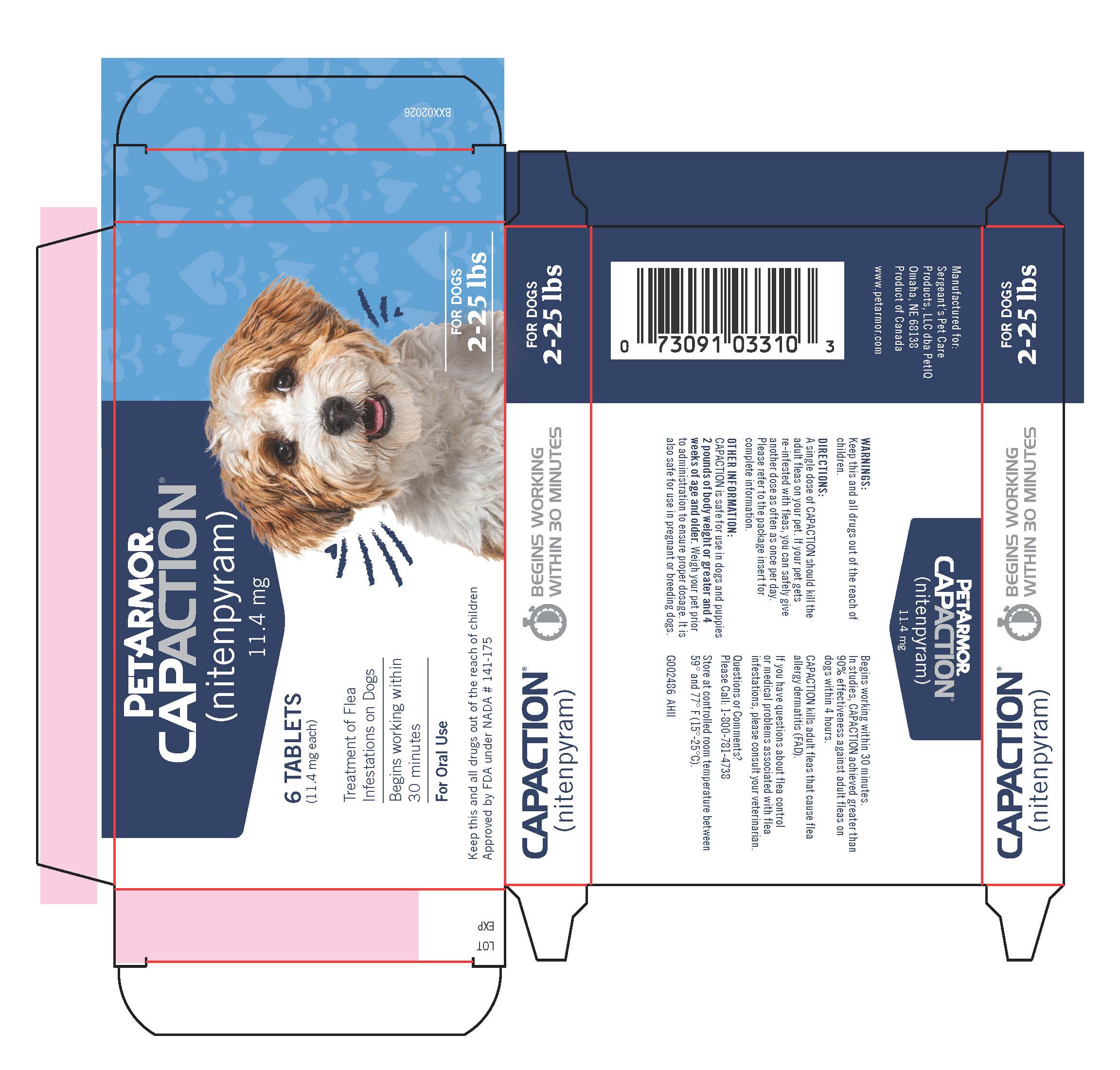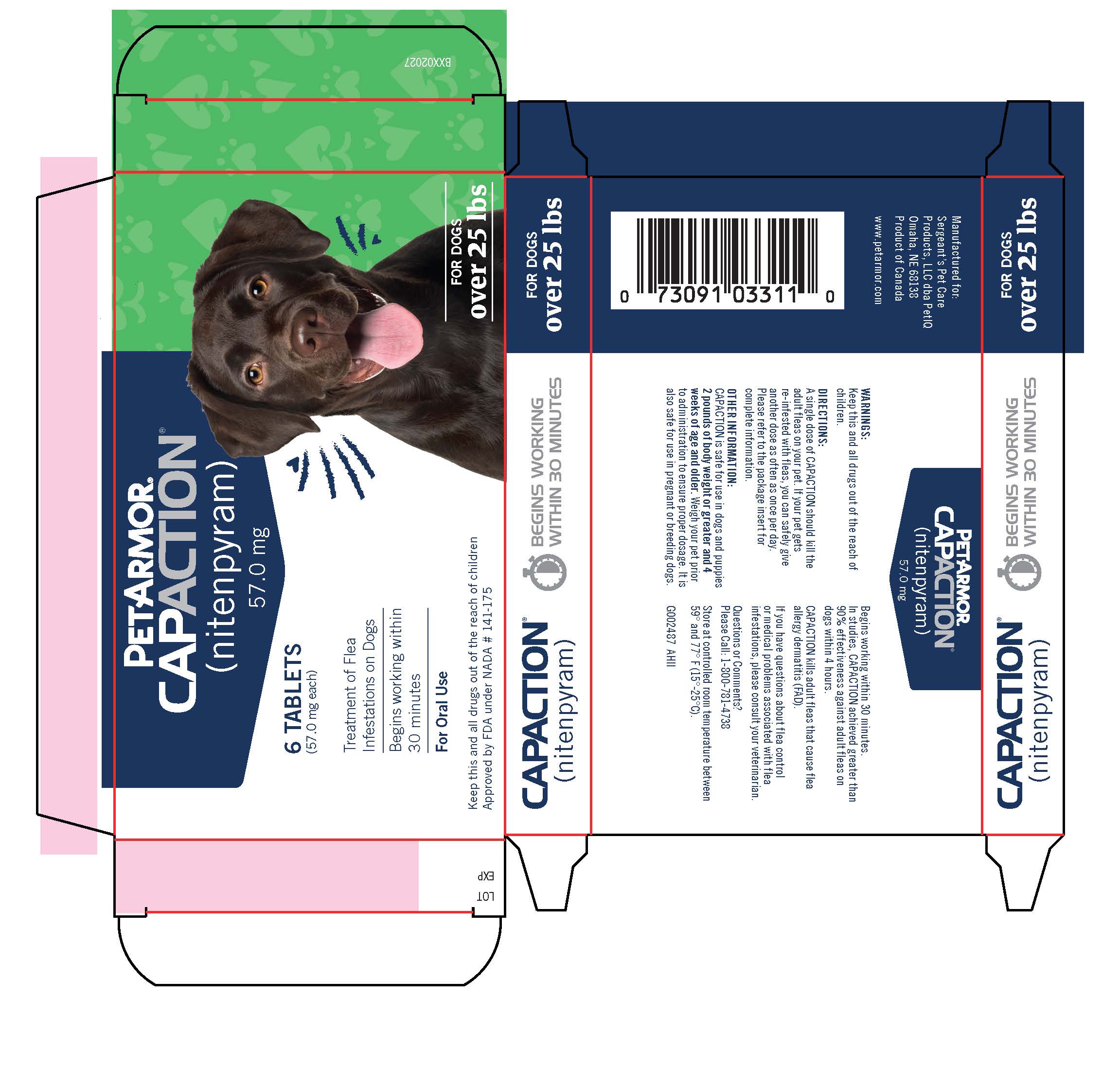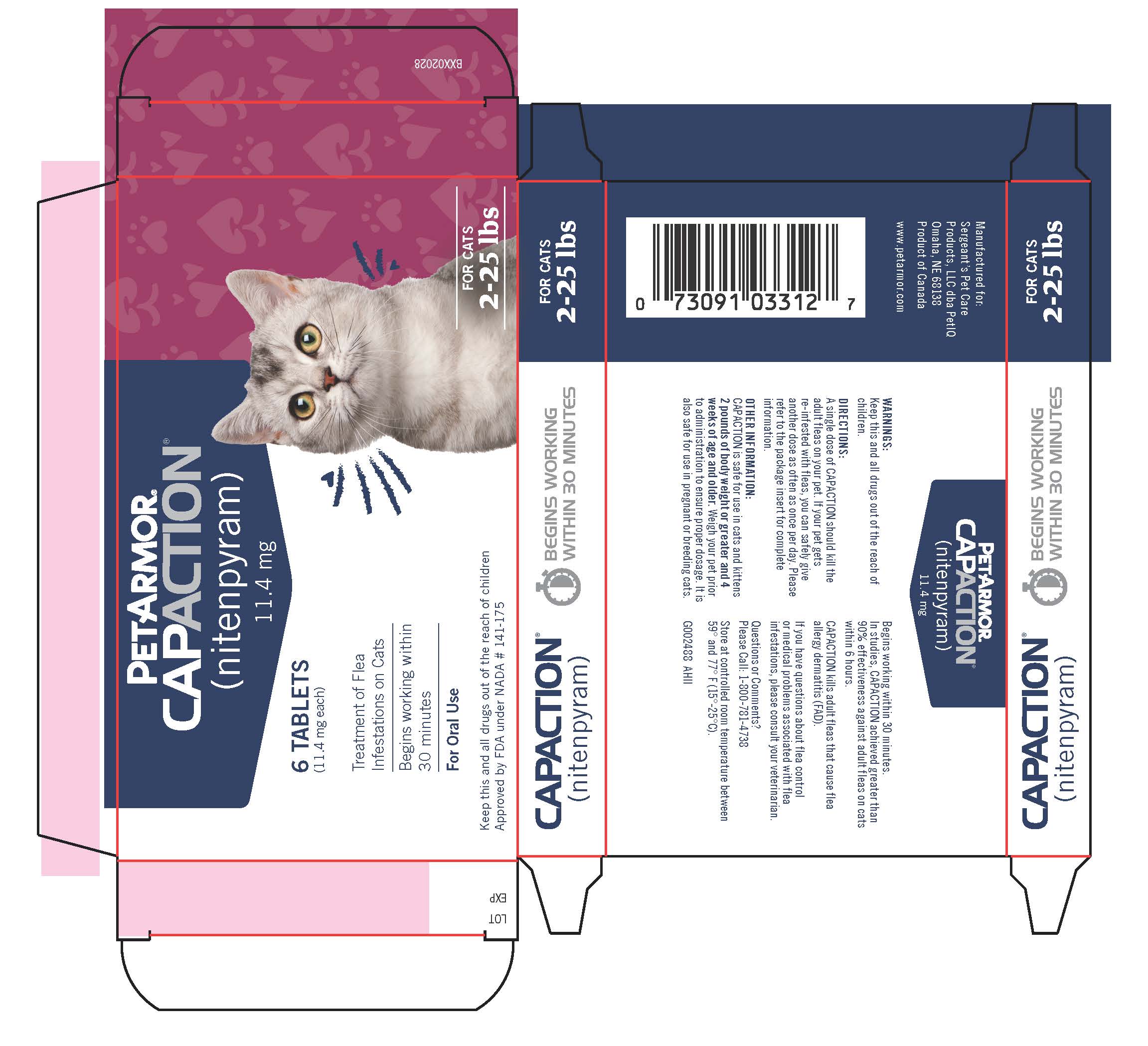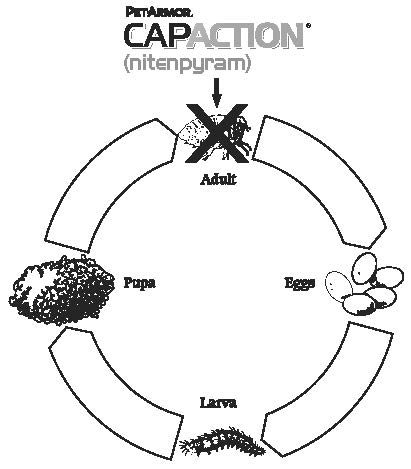 DRUG LABEL: PETARMOR CAPACTION
NDC: 21091-141 | Form: TABLET
Manufacturer: Sergeant's Pet Care Products LLC
Category: animal | Type: OTC ANIMAL DRUG LABEL
Date: 20251118

ACTIVE INGREDIENTS: NITENPYRAM 11.4 mg/1 1
INACTIVE INGREDIENTS: LACTOSE MONOHYDRATE; CELLULOSE, MICROCRYSTALLINE; STARCH, CORN; SILICON DIOXIDE; MAGNESIUM STEARATE

PETARMOR® CAPACTION®
(nitenpyram)

Capaction is an oral tablet for dogs, puppies, cats and kittens 2 pounds of body weight or greater and 4 weeks of age and older.

ACTIVE INGREDIENTS

CAPACTION Tablets contain 11.4 or 57.0 mg of nitenpyram, which belongs to the chemical class of neonicotinoids. Nitenpyram kills adult fleas.

WARNINGS

Not for human use. Keep this and all drugs out of the reach of children.

DIRECTIONS

CAPACTION Tablets kill adult fleas and are indicated for the treatment of flea infestations on dogs, puppies, cats and kittens 2 pounds of body weight or greater and 4 weeks of age and older.

A single dose of CAPACTION should kill the adult fleas on your pet. If your pet gets re-infested with fleas, you can safely give another dose as often as once per day.

To give CAPACTION Tablets, place the pill directly in your pet's mouth or hide it in food. If you hide the pill in food, watch closely to make sure your pet swallows the pill. If you are not sure that your pet swallowed the pill, it is safe to give a second pill.

Treat all infested pets in the household. Fleas can reproduce on untreated pets and allow infestations to persist.

DOSAGE
CAPACTION Tablets should be administered according to the following schedule. Weigh your pet prior to administration to ensure proper dosage. Do not administer to pets under 2 pounds.

Recommended Dosage Schedule
Species | Body Weight | Dose | Nitenpyram Per Tablet
Dog or Cat | 2-25 lbs. | One Tablet | 11.4 mg
Dog | 25.1-125 lbs. | One Tablet | 57.0 mg

ADVERSE REACTIONS

Pre-approval laboratory and clinical studies showed that CAPACTION Tablets are safe for use in dogs and cats, puppies and kittens 2 pounds of body weight or greater and 4 weeks of age and older. (See Post-Approval Experience section).

Post-Approval Experience (Rev. 2011):

The following adverse events are based on post-approval adverse drug experience reporting. Not all adverse reactions are reported to FDA CVM. It is not always possible to reliably estimate the adverse event frequency or establish a causal relationship to product exposure using this data. The following adverse events are listed in decreasing order of reporting frequency.

CATS: hyperactivity, panting, lethargy, itching, vocalization, vomiting, fever, decreased appetite, nervousness, diarrhea, difficulty breathing, salivation, incoordination, seizures, pupil dilation, increased heart rate, and trembling.

DOGS: lethargy/depression, vomiting, itching, decreased appetite, diarrhea, hyperactivity, incoordination, trembling, seizures, panting, allergic reactions including hives, vocalization, salivation, fever, and nervousness.

The frequency of serious signs, including neurologic signs and death, was greater in animals under 2 pounds of body weight, less than 8 weeks of age, and/or reported to be in poor body condition. In some instances, birth defects and fetal/neonatal loss were reported after treatment of pregnant and/or lactating animals.

To report adverse effects, access medical information, or obtain additional product information call 1-800-781-4738. For additional information about adverse drug experience reporting for animal drugs, contact FDA at 1-888-FDA-VETS or http://www.fda.gov/reportanimalae.

For a complete listing of adverse reactions for nitenpyram reported to the CVM see:

http://www.fda.gov/AnimalVeterinary/SafetyHealth/ProductSafetyInformation

OTHER INFORMATION

CAPACTION Tablets begin working within 30 minutes. In studies, CAPACTION achieved greater than 90% effectiveness against adult fleas on dogs within 4 hours and cats within 6 hours.

CAPACTION Tablets are safe for pregnant or nursing dogs and cats (See Post-Approval Experience section).

When using this product, you may notice that your dog or cat will start scratching itself as fleas begin to die. The scratching behavior is temporary and is a reaction to the fleas, not the drug. In cats and dogs, this may present as transient signs of hyperactivity, panting, vocalization and excessive grooming/licking.

CAPACTION Tablets kill adult fleas that cause flea allergy dermatitis (FAD).

CAPACTION Tablets may be used together with other products, including heartworm preventives, corticosteroids, antibiotics, vaccines, de-worming medications, shampoos and other flea products.

FLEA INFESTATIONS ON DOGS AND CATS

In addition to the common nuisance irritations associated with infestations, fleas can be responsible for skin conditions in your pet such as flea allergy dermatitis (FAD) in the dog and miliary dermatitis in the cat. Also, fleas transmit other parasites, including tapeworms. The control of flea infestations is important to your pet's health and also reduces the problems associated with these parasites.

CAPACTION Tablets do not have an effect on fleas in the pet's environment. You may need to treat more than one time because immature fleas in and around the home will continue to develop into adults that can reinfest your pet.

The following diagram illustrates the flea's life cycle and where CAPACTION Tablets work:

LIFE CYCLE OF FLEA

Fleas can be a problem because they reproduce so rapidly. A single female flea may produce up to 2,000 eggs over her lifetime. Eggs hatch and can develop into adults within only three weeks. Adult female fleas feed by ingesting blood from your pet and subsequently lay eggs, which drop off your pet's coat. Within days, larvae hatch from the eggs and live undetected in your pet's surroundings, such as the carpet, bedding and other protected areas. Flea larvae spin a cocoon, and, when appropriately stimulated, a young adult flea emerges and jumps onto your pet to continue the life cycle. When these new fleas are seen on your pet, treat with CAPACTION Tablets.

After reading this insert, if you have any questions about flea control or medical problems associated with flea infestations, consult your veterinarian, who is your pet's health care expert.

STORAGE CONDITIONS

Store at controlled room temperature, between 59° and 77°F (15°-25°C).

For questions, comments, technical assistance or to report a suspected adverse event please call 1-800-781-4738

Approved by FDA under NADA # 141-175

PETIQ